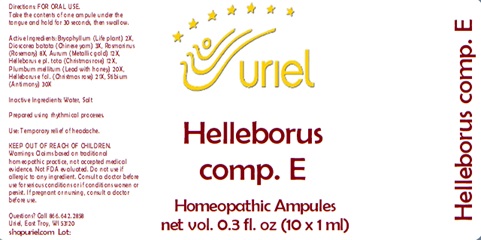 DRUG LABEL: Helleborus comp. E
NDC: 48951-5121 | Form: LIQUID
Manufacturer: Uriel Pharmacy Inc.
Category: homeopathic | Type: HUMAN OTC DRUG LABEL
Date: 20241217

ACTIVE INGREDIENTS: HELLEBORUS NIGER ROOT 21 [hp_X]/1 mL; ANTIMONY 30 [hp_X]/1 mL; KALANCHOE DAIGREMONTIANA LEAF 2 [hp_X]/1 mL; HELLEBORUS FOETIDUS ROOT 12 [hp_X]/1 mL; ROSMARINUS OFFICINALIS FLOWERING TOP 8 [hp_X]/1 mL; LEAD 20 [hp_X]/1 mL; CHINESE YAM 3 [hp_X]/1 mL; GOLD 12 [hp_X]/1 mL
INACTIVE INGREDIENTS: SODIUM CHLORIDE; WATER

Helleborus comp. E

INDICATIONS AND USAGE

Directions: FOR ORAL USE.

DOSAGE AND ADMINISTRATION

Take the contents of one ampule under the tongue and hold for 30 seconds, then swallow.

ACTIVE INGREDIENT

Active Ingredients: Bryophyllum (Life plant) 2X, Dioscorea batata (Chinese yam) 3X, Rosmarinus (Rosemary) 8X, Aurum (Metallic gold) 12X, Helleborus e pl. tota (Christmas rose) 12X, Plumbum mellitum (Lead with honey) 20X, Helleborus e fol. (Christmas rose) 21X, Stibium (Antimony) 30X

Inactive Ingredients: Water, Salt

Prepared using rhythmical processes.

PURPOSE

Use: Temporary relief of headache.

KEEP OUT OF REACH OF CHILDREN.

WARNINGS

Warnings: Claims based on traditional homeopathic practice, not accepted medical evidence. Not FDA evaluated. Do not use if allergic to any ingredient. Consult a doctor before use for serious conditions or if conditions worsen or persist. If pregnant or nursing, consult a doctor before use.

Questions? Call 866.642.2858
Uriel, East Troy, WI 53120
shopuriel.com Lot: